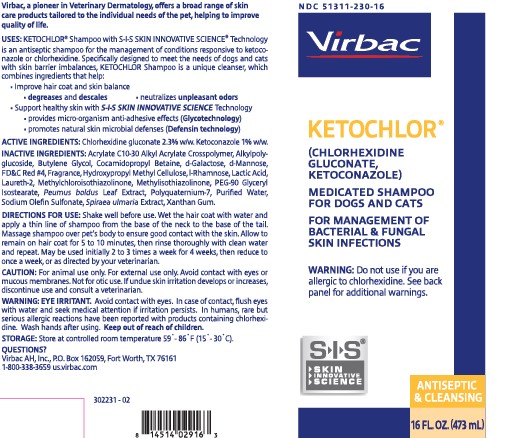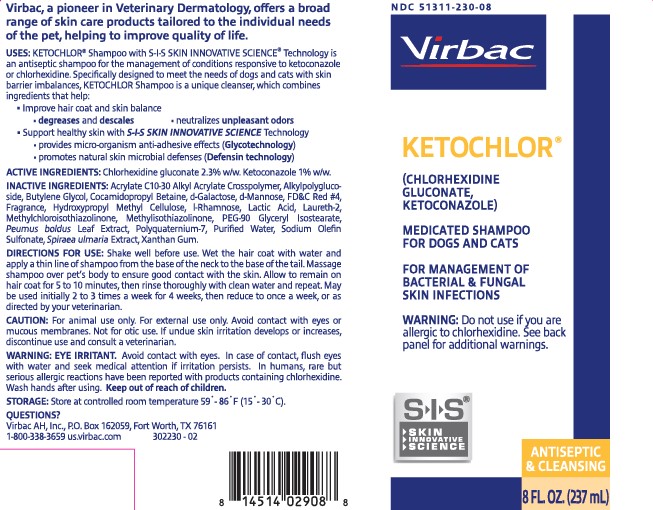 DRUG LABEL: KETOCHLOR
NDC: 51311-230 | Form: SHAMPOO
Manufacturer: Virbac AH, Inc.
Category: animal | Type: OTC ANIMAL DRUG LABEL
Date: 20240229

ACTIVE INGREDIENTS: CHLORHEXIDINE GLUCONATE 23 mg/1 mL; KETOCONAZOLE 10 mg/1 mL

KETOCHLOR® (chlorhexidine gluconate, ketoconazole)

MEDICATED SHAMPOO FOR DOGS AND CATS FOR MANAGEMENT OF BACTERIAL & FUNGAL SKIN INFECTIONS S-I-S® - SKIN - INNOVATIVE - SCIENCE ANTISEPTIC & CLEANSING Virbac, a pioneer in Veterinary Dermatology, offers a broad range of skin care products tailored to the individual needs of the pet, helping to improve quality of life.

USES:

KETOCHLOR® Shampoo with S-I-S SKIN INNOVATIVE SCIENCE® Technology is an antiseptic shampoo for the management of conditions responsive to ketoconazole or chlorhexidine. Specifically designed to meet the needs of dogs and cats with skin barrier imbalances, KETOCHLOR Shampoo is a unique cleanser, which combines ingredients that help:

● Improve hair coat and skin balance:
degreases and descales
neutralizes unpleasant odors

● Support healthy skin with S-I-S SKIN INNOVATIVE SCIENCE Technology
provides micro-organism anti-adhesive effects (Glycotechnology)
promotes natural skin microbial defenses (Defensin technology)

WARNING:

Do not use if you are allergic to chlorhexidine. See back panel for additional warnings.

ACTIVE INGREDIENTS:

Chlorhexidine gluconate 2.3% w/w, Ketoconazole 1% w/w.

INACTIVE INGREDIENTS:

Acrylate C10-30 Alkyl Acrylate Crosspolymer, Alkylpolyglucoside, Butylene Glycol, Cocomidopropyl Betaine, d-Galactose, d-Mannose, FD&C Red #4, Fragrance, Hydroxypropyl Methyl Cellulose, l-Rhamnose, Lactic Acid, Laureth-2, Methylchloroisothiazolinone, Methylisothiazolinone, PEG-90 Glyceryl Isostearate, Peumus boldus Leaf Extract, Polyquaternium-7, Purified Water, Sodium Olefin Sulfonate, Spiraea ulmaria Extract, Xanthan Gum.

DIRECTIONS FOR USE:

Shake well before use. Wet the hair coat with water and apply a thin line of shampoo from the base of the neck to the base of the tail. Massage shampoo over pet’s body to ensure good contact with the skin. Allow to remain on hair coat for 5 to 10 minutes, then rinse thoroughly with clean water and repeat. May be used initially 2 to 3 times a week for 4 weeks, then reduce to once a week, or as directed by your veterinarian.

CAUTION:

For animal use only. For external use only. Avoid contact with eyes or mucous membranes. Not for otic use. If undue skin irritation develops or increases, discontinue use and consult a veterinarian.

WARNING: EYE IRRITANT.

Avoid contact with eyes. In case of contact, flush eyes with water and seek medical attention if irritation persists. In humans, rare but serious allergic reactions have been reported with products containing chlorhexidine. Wash hands after using. Keep out of reach of children.

STORAGE:

Store at controlled room temperature 59°- 86° F (15°- 30° C).

QUESTIONS?

Virbac AH, Inc., P.O. Box 162059, Fort Worth, TX 76161

1-800-338-3659

us.virbac.com

302230-02

302231-02